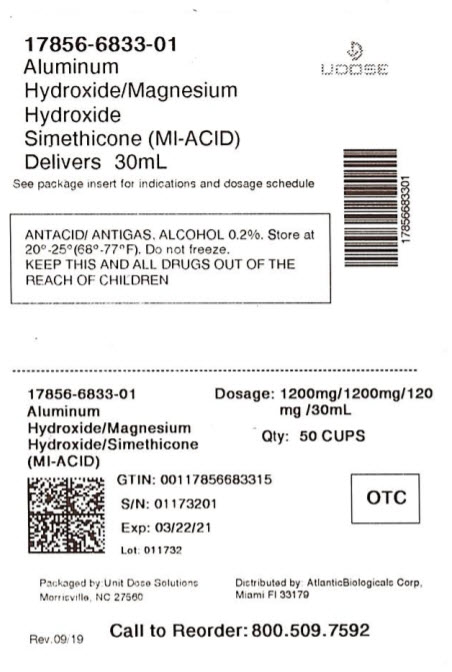 DRUG LABEL: Mi Acid
NDC: 17856-6833 | Form: SUSPENSION
Manufacturer: ATLANTIC BIOLOGICALS CORP.
Category: otc | Type: HUMAN OTC DRUG LABEL
Date: 20200923

ACTIVE INGREDIENTS: ALUMINUM HYDROXIDE 400 mg/10 mL; MAGNESIUM HYDROXIDE 400 mg/10 mL; DIMETHICONE 40 mg/10 mL
INACTIVE INGREDIENTS: SILICON DIOXIDE; BUTYLPARABEN; HYPROMELLOSES; CELLULOSE, MICROCRYSTALLINE; CARBOXYMETHYLCELLULOSE SODIUM; PEPPERMINT OIL; PROPYLPARABEN; WATER; SORBITOL

Major Pharmaceuticals Mi-Acid™ Drug Facts

Active ingredients (in each 10 mL)

Aluminum hydroxide (equiv. to dried gel, USP) 400 mg

Magnesium hydroxide 400 mg

Simethicone 40 mg

Purposes

Antacid

Antigas

Uses

relieves

- heartburn
- acid indigestion
- sour stomach
- upset stomach due to these symptoms
- pressure and bloating commonly referred to as gas

Warnings

Ask a doctor before use if you have

- kidney disease
- a magnesium-restricted diet

Ask a doctor or pharmacist before use if you are

presently taking a prescription drug. Antacids may interact with certain prescription drugs.

When using this product

do not exceed 120 mL in a 24-hour period, or use the maximum dosage for more than 2 weeks, unless directed by a doctor

Keep out of reach of children.

In case of overdose, get medical help or contact a Poison Control Center right away (1-800-222-1222).

Directions

- shake well before use
- measure with dosing cup provided
- adults and children 12 years and over: 10 mL – 20 mL between meals, at bedtime or as directed by a doctor
- do not take more than 120 mL in any 24 hour period
- do not use the maximum dosage for more than 2 weeks
- children under 12 years: ask a doctor
- mL = milliliter

Other information

- each 10 mL contains: magnesium 175 mg
- does not meet USP requirements for preservative effectiveness
- store at 20-25°C (68-77°F), do not freeze

Inactive ingredients

butylparaben, flavor, hypromellose, microcrystalline cellulose and carboxymethylcellulose sodium, peppermint oil, propylparaben, purified water, simethicone emulsion, sorbitol, sorbitol solution

Questions or comments?

1-800-616-2471

Principal Display Panel

FAST ACTING

MI-ACID™

Regular Strength

ANTACID / ANTIGAS

CLASSIC

SOOTHING RELIEF OF:

HEARTBURN

ACID INDIGESTION

SOUR STOMACH

ALCOHOL 0.2%